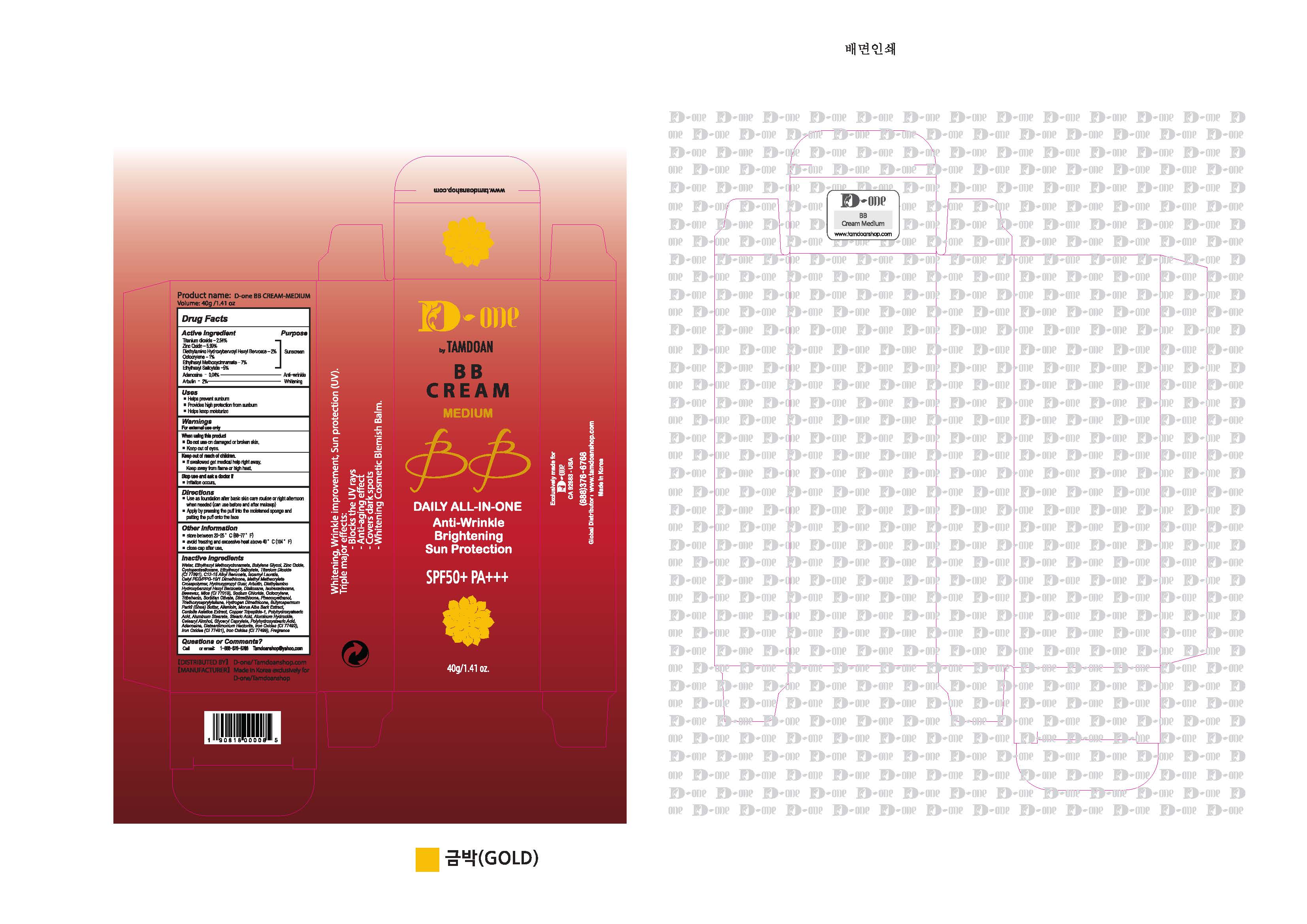 DRUG LABEL: D-ONE BY TAMDOAN BB MEDIUM
NDC: 70931-0003 | Form: CREAM
Manufacturer: DRAN CO.,LTD
Category: otc | Type: HUMAN OTC DRUG LABEL
Date: 20191118

ACTIVE INGREDIENTS: TITANIUM DIOXIDE 2.54 g/100 g; ZINC OXIDE 5.99 g/100 g; DIETHYLAMINO HYDROXYBENZOYL HEXYL BENZOATE 2 g/100 g; OCTOCRYLENE 1 g/100 g; OCTINOXATE 7 g/100 g; OCTISALATE 5 g/100 g; ADENOSINE 0.04 g/100 g; ARBUTIN 2 g/100 g
INACTIVE INGREDIENTS: WATER; BUTYLENE GLYCOL; ALLANTOIN

Drug Facts

ACTIVE INGREDIENT

Titanium dioxide, Zinc Oxide, Diethylamino Hydroxybenzoyl Hexyl Benzoate, Octocrylene, Ethylhexyl Methoxycinnamate, Ethylhexyl Salicylate, Adenosine, Arbutin

INACTIVE INGREDIENT

Water, Butylene Glycol, Allantoin, Etc.

PURPOSE

- Helps prevent sunburn
- Provides high protection from sunburn
- Helps keep moisturize

keep out of reach of the children

INDICATIONS AND USAGE

- Use as foundation after basic skin care routine or right afternoon when needed (can use before and after makeup)
- Apply by pressing the puff into the moistened sponge and patting the puff onto the face

WARNINGS

1. Do not use in the following cases(Eczema and scalp wounds)
2.Side Effects
1)Due to the use of this product, if rash, irritation, itching and symptopms of hypersnesitivity occur dicontinue use and consult your pharmacist or doctor
3.General Precautions
1)If in contact with the eyes, wash out thoroughty with water If the symptoms are servere, seek medical advice immediately
2)This product is for exeternal use only. Do not use for internal use
4.Storage and handling precautions
1)If possible, avoid direct sunlight and store in cool and area of low humidity
2)In order to maintain the quality of the product and avoid misuse
3)Avoid placing the product near fire and store out in reach of children

DOSAGE AND ADMINISTRATION

for external use only